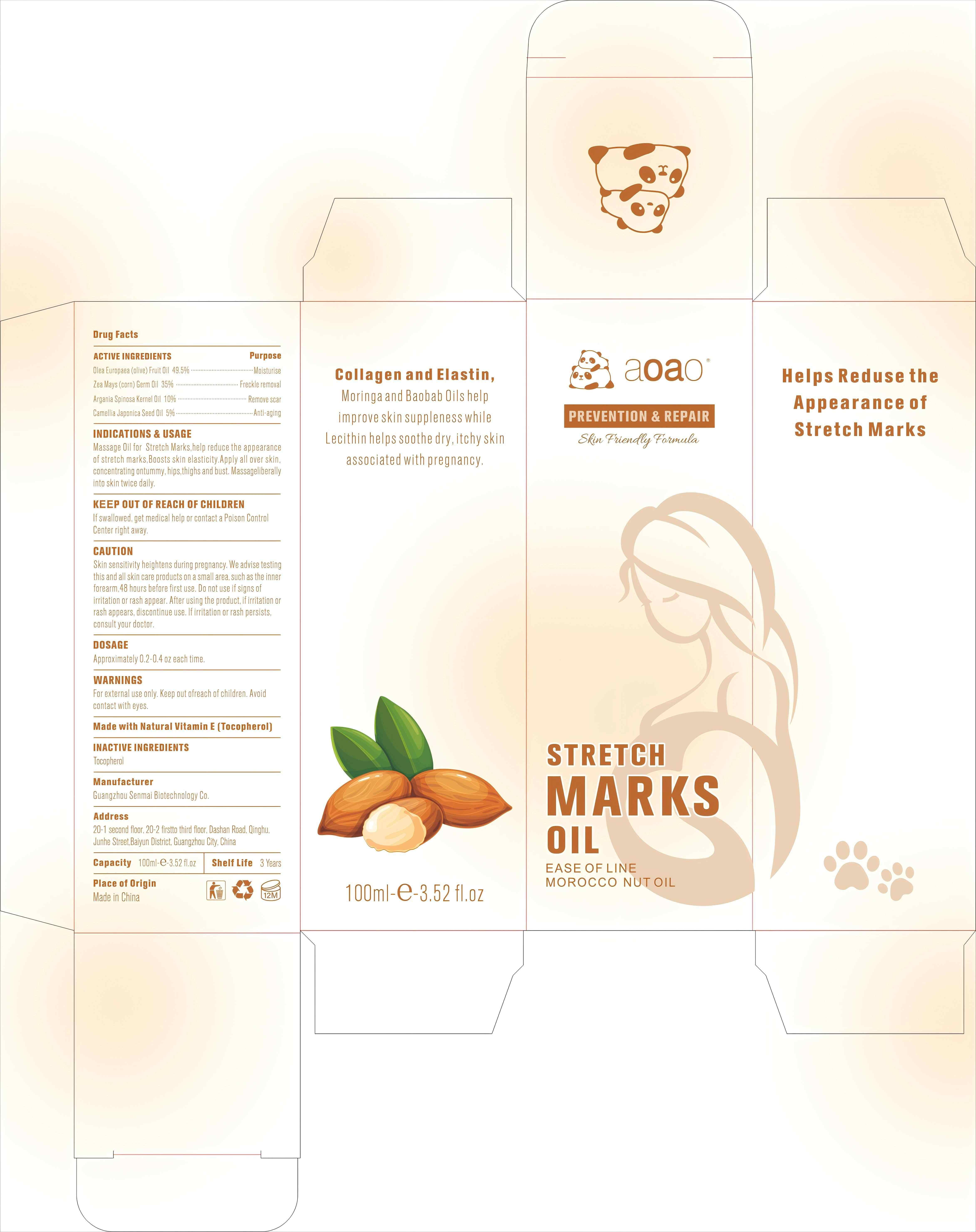 DRUG LABEL: Stretch Marks Oil
NDC: 84509-007 | Form: OIL
Manufacturer: Guangzhou Senmai Biotechnology Co.
Category: otc | Type: HUMAN OTC DRUG LABEL
Date: 20240731

ACTIVE INGREDIENTS: CORN OIL 35000 mg/100 mL; OLIVE OIL 49500 mg/100 mL; ARGAN OIL 10000 mg/100 mL; CAMELLIA JAPONICA SEED OIL 5000 mg/100 mL
INACTIVE INGREDIENTS: TOCOPHEROL 500 mg/100 mL

Active Ingredients

Olea Europaea (Olive) Fruit Oil 49.5%
Zea Mays (Corn) Germ Oil 35%
Argania Spinosa Kernel Oil 10%
Camellia Japonica Seed Oil 5%

Purpose

Moisturise,Freckle removal ,Remove scar,Anti-aging,Anti-wrinkle.

INDICATIONS & USAGE

Massage Oil for Stretch Marks,help reduce the appearance of stretch marks,Boosts skin elasticity.Apply all over skin, concentrating ontummy, hips,thighs and bust. Massageliberally into skin twice daily.

Keep out of reach of children

If swallowed, get medical help or contact a Poison Control Center right away

CAUTION

Skin sensitivity heightens during pregnancy. We advise testing this and all skin care products on a small area, such as the inner forearm,48 hours before first use. Do not use if signs ofirritation or rash appear. After using the product, if irritation or rash appears, discontinue use. lf irritation or rash persists, consult your doctor.

DOSAGE

Approximately 0.2-0.4 oz each time.

Warnings

For external use only. Keep out ofreach of children.Avoid contact with eyes.

DESCRIPTION

Made with Natural Vitamin E (Tocopherol)

Inactive Ingredients

Tocopherol .

Manufacturer

Guangzhou Senmai Biotechnology Co.

Address

20-1second floor, 20-2 first to third floor,Dashan Road,Qinghu,Junhe Street, Baiyun district, Guangzhou City, China.

Capacity

100ml/3.52 Fl.oz

Shelf Life

3 Years

Place of Origin

Made in China